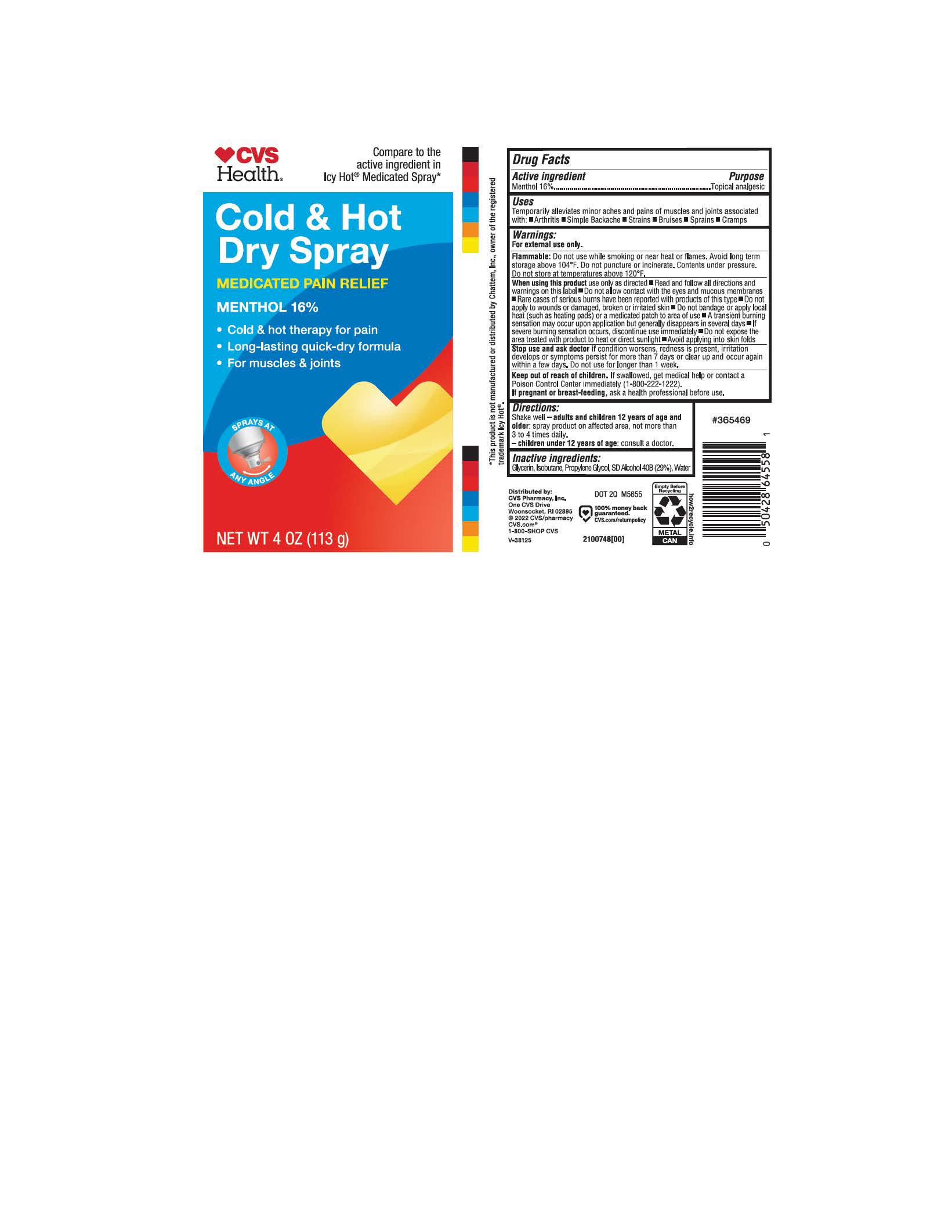 DRUG LABEL: CVS cold and Hot
NDC: 51316-899 | Form: SPRAY
Manufacturer: CVS
Category: otc | Type: HUMAN OTC DRUG LABEL
Date: 20251229

ACTIVE INGREDIENTS: MENTHOL 16 g/100 g
INACTIVE INGREDIENTS: WATER; GLYCERIN; ISOBUTANE; PROPYLENE GLYCOL; DEHYDRATED ALCOHOL

CVS cold and Hot Spray

ACTIVE INGREDIENT

Menthol 16%

PURPOSE

Topical analgesic

INDICATIONS AND USAGE

Temporarily alleviates minor aches and pains of muscles and joints associated with

Arthritis

Simple Backache

Strains

Bruises

Cramps

WARNINGS

For external use only

Flammable:

Do not use while smoking or near heat or flames. Avoid longterm storage above 104°F. Do not punctuate or incinerate. Contents under pressure. Do not store at temperatures above 120°F.

When using this product use only as directed

Read and follow all directions and warnings on this label

Do not allow contact with eyes and mucous membranes

Rare cases of serious burns have been reported with products of this type

Do not apply to wounds or damaged, broken or irritated skin

Do not bandage or apply local heat (such as heating pads) or medicated patch to the area of use

A transient burning sensation may occur upon application but generally disappears in several days

If severe burning sensations occurs, discontinue use immediately

Do not expose the area treated with product to heat or direct sunlight

Avoid applying into skin folds

Stop use and ask doctor if condition worsens, redness is present, irritation develops or symptoms persist for more than 7 days or clear up and occur again within few days. Do not use for longer than 1 week.

Keep out of reach of children. If swallowed, get medical help or contact a Poison Control Center immediately (1-800-222-1222).

PREGNANCY OR BREAST FEEDING

If pregnant or breast-feeding, ask a health professional before use.

Directions:

Shake well - adults and children 12 years of age and older: spray product on affected area, not more than 3 to 4 times daily.

- children under 12 years of age: consult a doctor.

INACTIVE INGREDIENT

Glycerin, Isobutane, Propylene Glycol, SD Alcohol 40B (29%), Water